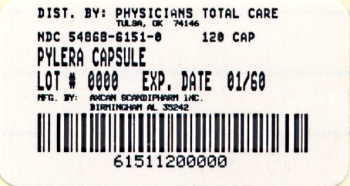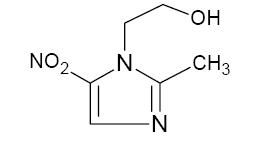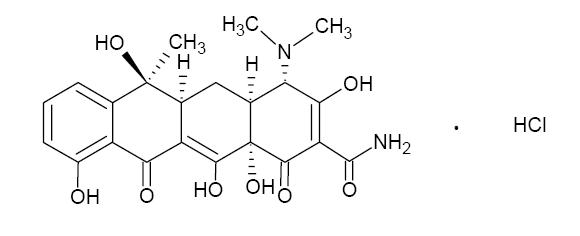 DRUG LABEL: Pylera
NDC: 54868-6151 | Form: CAPSULE
Manufacturer: Physicians Total Care, Inc.
Category: prescription | Type: HUMAN PRESCRIPTION DRUG LABEL
Date: 20110203

ACTIVE INGREDIENTS: Bismuth subcitrate potassium 140 mg/1 1; Metronidazole 125 mg/1 1; Tetracycline hydrochloride 125 mg/1 1
INACTIVE INGREDIENTS: MAGNESIUM STEARATE; LACTOSE MONOHYDRATE; TALC; GELATIN; TITANIUM DIOXIDE

HIGHLIGHTS OF PRESCRIBING INFORMATION

These highlights do not include all the information needed to use PYLERA safely and effectively. See full prescribing information for PYLERA. Initial U.S. Approval: 2006

MICROBIOLOGY

To reduce the development of drug-resistant bacteria and maintain the effectiveness of PYLERA and other antibacterial drugs, PYLERA should be used only to treat or prevent infections that are proven or strongly suspected to be caused by bacteria. (1)

1 INDICATIONS AND USAGE

PYLERA is a combination antibacterial indicated for the treatment of patients with Helicobacter pylori infection and duodenal ulcer disease (active or history of within the past 5 years) to eradicate H. pylori. (1.1)

2 DOSAGE AND ADMINISTRATION

- Each dose of PYLERA includes 3 capsules. (2)
- Each dose of PYLERA should be taken 4 times a day, after meals and at bedtime for 10 days. (2)
- Administer PYLERA with omeprazole 20 mg twice daily (after the morning and evening meals). (2)

3 DOSAGE FORMS AND STRENGTHS

Each capsule of PYLERA contains: (3)

- 140 mg of bismuth subcitrate potassium
- 125 mg of metronidazole
- 125 mg of tetracycline hydrochloride

4 CONTRAINDICATIONS

- Patients with renal impairment. (4.4)
- Patients with known hypersensitivity to product components. (4.5)

5 WARNINGS AND PRECAUTIONS

- Fetal Toxicity: Advise pregnant women of the risk for permanent discoloration of teeth with tetracycline if used during the second or third trimester (5.1, 8.1)
- Maternal Toxicity: Risk of hepatotoxicity in pregnant women with high doses of intravenous tetracycline also resulting in stillborn or premature birth (5.2, 8.1)
- Central and Peripheral Nervous System Effects: encephalopathy and peripheral neuropathy with metronidazole, pseudotumor cerebri with tetracycline and neurotoxicity with bismuth-containing products; Monitor patients with CNS conditions closely and discontinue promptly if abnormal neurologic signs develop. (5.4)
- Development of Superinfection: If superinfection occurs, discontinue PYLERA and institute appropriate therapy. (5.5)
- Photosensitivity: avoid exposure to sun and sun lamps. (5.6)

6 ADVERSE REACTIONS

Most frequently reported adverse reactions (≥5%); abnormal feces, diarrhea, nausea, and headache. (6.1)

To report SUSPECTED ADVERSE REACTIONS, contact AXCAN Pharma US, Inc. at 1-800-472-2634 or FDA at 1-800-FDA-1088 or www.fda.gov/medwatch.

7 DRUG INTERACTIONS

- Methoxyflurane: Risk of fatal renal toxicity; do not co-administer. (4.1, 7.1)
- Disulfiram: Psychotic reactions can occur; do not take concurrently or within the last 2 weeks of disulfiram. (4.2, 7.2)
- Alcohol: Abdominal cramps, nausea, vomiting, headaches, and flushing can occur; do no consume during therapy and for at least 3 days afterwards. (7.3)
- Oral Contraceptives: Decreased efficacy possibly resulting in pregnancy; use a different or additional form of contraception. (7.4)
- Anticoagulants: Potentiation of the anticoagulant effect; Prothrombin time, International Normalized Ratio (INR), or other suitable anticoagulation tests should be closely monitored. (7.5)
- Lithium: Increased lithium serum concentrations; measure serum lithium and serum creatinine concentrations during therapy. (7.6)
- Antacids, Multivitamins or Dairy Products: Decreased absorption of PYLERA; do not take concomitantly. (7.7)

8 USE IN SPECIFIC POPULATIONS

- Nursing Mothers: Discontinue drug or nursing taking into consideration the importance of the drug to the mother. (8.3)
- Pediatric Use: Tetracycline may cause permanent discoloration of the teeth. Enamel hypoplasia has also been reported. Do not use in children less than 8 years of age. (5.3,8.4)

FULL PRESCRIBING INFORMATION

1 INDICATIONS AND USAGE

To reduce the development of drug-resistant bacteria and maintain the effectiveness of PYLERA and other antibacterial drugs, PYLERA should be used only to treat or prevent infections that are proven or strongly suspected to be caused by susceptible bacteria. When culture and susceptibility information are available, they should be considered in selecting or modifying antibacterial therapy. In the absence of such data, local epidemiology and susceptibility patterns may contribute to the empiric selection of therapy.

1.1 Eradication of Helicobacter pylori in Patients with Active Duodenal Ulcer or History of Duodenal Ulcer Disease

PYLERA in combination with omeprazole are indicated for the treatment of patients with Helicobacter pylori infection and duodenal ulcer disease (active or history of within the past 5 years) to eradicate H. pylori. The eradication of Helicobacter pylori has been shown to reduce the risk of duodenal ulcer recurrence.

2 DOSAGE AND ADMINISTRATION

Each dose of PYLERA is 3 capsules. Each dose of all 3 capsules should be taken 4 times a day, after meals and at bedtime for 10 days. One omeprazole 20 mg capsule should be taken twice a day with PYLERA after the morning and evening meal for 10 days (Table 1).

Table 1: Daily Dosing Schedule for PYLERA
Time of dose | Number of capsules of PYLERA | Number of capsules of Omeprazole 20 mg
After morning meal | 3 | 1
After lunch | 3 | 0
After evening meal | 3 | 1
At bedtime | 3 | 0

Instruct patients to swallow the PYLERA capsules whole with a full glass of water (8 ounces). Ingestion of adequate amounts of fluid, particularly with the bedtime dose, is recommended to reduce the risk of esophageal irritation and ulceration by tetracycline hydrochloride.

If a dose is missed, patients should continue the normal dosing schedule until medication is gone. Patients should not take double doses. If more than 4 doses are missed, the prescriber should be contacted.

3 DOSAGE FORMS AND STRENGTHS

Each PYLERA capsule contains 140 mg of bismuth subcitrate potassium, 125 mg of metronidazole, and a smaller capsule inside containing 125 mg of tetracycline hydrochloride. The capsules are white and opaque, with the Axcan Pharma logo printed on the body and “BMT” printed on the cap.

4 CONTRAINDICATIONS

4.1 Methoxyflurane

Do not administer methoxyflurane to patients taking PYLERA. The concurrent use of tetracycline hydrochloride, a component of PYLERA, with methoxyflurane has been reported to result in fatal renal toxicity [See Drug Interactions (7.1)].

4.2 Disulfiram

PYLERA is contraindicated in patients who have taken disulfiram within the last two weeks. Psychotic reactions have been reported in alcoholic patients who are using metronidazole, a component of PYLERA, and disulfiram concurrently [See Drug Interactions (7.2)].

4.3 Alcohol

Alcoholic beverages or other products containing propylene glycol should not be consumed during and for at least 3 days after therapy with PYLERA. A disulfiram-like reaction (abdomincal cramps, nausea, vomiting, headaches, and flushing) may occur due to the interaction between alcohol or propylene glycol and metronidazole, a component of PYLERA [See Drug Interactions (7.3].

4.4 Renal Impairment

PYLERA is contraindicated in patients with severe renal impairment. The antianabolic action of the tetracyclines may cause an increase in blood urea nitrogen (BUN) [See Adverse Reactions (6.3)]. In patients with significantly impaired renal function, higher serum concentrations of tetracyclines may lead to azotemia, hyperphosphatemia, and acidosis.

4.5 Hypersensitivity Reactions

PYLERA is contraindicated in patients with known hypersensitivity (e.g. urticaria, erythematous rash, flushing, and fever) to bismuth subcitrate potassium, metronidazole or other nitroimidazole derivatives, or tetracycline [See Adverse Reactions (6.3)].

5 WARNINGS AND PRECAUTIONS

5.1 Fetal Toxicity

There are no adequate and well-controlled studies of PYLERA in pregnant women. However, tetracycline can cause fetal harm when administered to a pregnant women. The use of drugs of the tetracycline class during the second and third trimester pregnancy can also cause permanent discoloration of the teeth (yellow-gray brown) and possibly inhibit bone development [See Warnings and Precautions (5.3)]. Administration of oral tetracycline to pregnant rats at various doses resulted in yellow fluorescence in teeth and bones in newborn animals. If this drug is used during pregnancy, or if the patient becomes pregnant while taking this drug, the patient should be apprised of the potential hazard to the fetus [See Use in Specific Populations (8.1)]

5.2 Maternal Toxicity

Tetracycline administered during pregnancy at high doses (> 2 g IV) was associated with rare but serious cases of maternal hepatotoxicity. This syndrome may result in stillborn or premature birth due to maternal pathology [See Use in Specific Populations (8.3)].

5.3 Tooth Enamel Discoloration and Hypoplasia

The use of drugs of the tetracycline class during tooth development (last half of pregnancy, infancy, and childhood to the age of 8 years) may cause permanent discoloration of the teeth (yellow-gray brown). This adverse reaction is more commom during long-term use of the drug, but has been observed following repeated short-courses. Enamel hypoplasia has also been reported. PYLERA, therefore, should not be used in this age group unless other drugs are not likely to be effective or are contraindicated [See Use in Specific Populations (8.4)] .

5.4 Central and Peripheral Nervous System Effects

Metronidazole: Cases of encephalopathy and peripheral neuropathy (including optic neuropathy) have been reported with metronidazole: Encephalopathy has been reported in association with cerebellar toxicity characterized by ataxia, dizziness, and dysarthria. CNS lesions seen on MRI have been described in reports of encephalopathy. CNS symptoms are generally reversible within days to weeks upon discontinuation of metronidazole. CNS lesions seen on MRI have also been described as reversible; Peripheral neuropathy, mainly of sensory type has been reported and is characterized by numbness or paresthesia of an extremity.

Convulsive seizures have been reported in patients treated with metronidazole.

Aseptic meningitis: Cases of aseptic meningitis have been reported with metronidazole. Symptoms can occur within hours of dose adiminstration and generally resolve after metronidazole therapy is discontinued.

Tetracycline: Cases of pseudotumor cerebri in adults have been associated with the use of tetracycline. The usual clinical manifestations are headache and blurred vision. While this condition and related symptoms usually resolve soon after discontinuation of the tetracycline, the possibility for permanent sequelae exists.

Bismuth-containing products: Cases of neurotoxicity associated with excessive doses of various bismuth-containing products have been reported. Effects have been reversible with discontinuation of bismuth therapy.

The appearance of abnormal neurologic signs and symptoms demands the prompt evaluation of the benefit/risk ratio of the continuation of PYLERA therapy [See Adverse Reactions (6.3)]

5.5 Development of Superinfections

Known or previously unrecognized candidiasis may present more prominent symptoms during therapy with metronidazole and requires treatment with an antifungal agent.

As with other antibiotics, use of tetracycline hydrochloride may result in overgrowth of nonsusceptible organisms, including fungi. If superinfection occurs, discontinue PYLERA and institute appropriate therapy

5.6 Photosensitivity

Photosensitivity, manifested by an exaggerated sunburn reaction, has been observed in patients taking tetracycline [See Adverse Reactions (6.3)]. Patients apt to be exposed to direct sunlight or ultraviolet light should be advised that this reaction can occur with tetracycline drugs. Instruct patients taking PYLERA to avoid exposure to the sun or sun lamps. Discontinue treatment at the first evidence of skin erythema.

5.7 Darkening of the Tongue and/or Black Stool

Bismuth subcitrate potassium may cause temporary and harmless darkening of the tongue and/or black stool, generally reversible within several days after treatment is stopped [See Adverse Reactions (6.1)]. Stool darkening should not be confused with melena.

5.8 Use in Patients with Blood Dyscrasias

Metronidazole is a nitroimidazole, and should be used with care in patients with evidence or history of blood dyscrasia. A mild leukopenia has been observed during its administration; however, no persistent hematologic abnormalities attributable to metronidazole have been observed in clinical studies. Total and differential leukocyte counts are recommended before and after therapy [See Adverse Reactions (6.3)].

5.9 Laboratory Test Interactions

Bismuth absorbs x-rays and may interfere with x-ray diagnostic procedures of the gastrointestinal tract.

Bismuth subcitrate potassium may cause a temporary and harmless darkening of the stool. However, this change does not interfere with standard tests for occult blood.

Metronizadole may interfere with certain types of determinations of serum chemistry values, such as aspartate aminotransferase (AST, SGOT), alanine aminotransferase (ALT, SGPT), lactate dehydrogenase (LDH), triglycerides, and hexokinase glucose. Values of zero may be observed. All of the assays in which interference has been reported involve enzymatic coupling of the assay to oxidation-reduction of nicotinamide (NAD+ <=> NADH). Interference is due to the similarity in absorbance peaks of NADH (340 nm) and metronidazole (322 nm) at pH 7

5.10 Development of Drug Resistant Bacteria

Prescribing PYLERA in the absence of a proven or strongly suspected bacterial infection or a prophylactic indication is unlikely to provide benefit to the patient and increases the risk of the development of drug-resistant bacteria.

6 ADVERSE REACTIONS

6.1 Clinical Trials Experience

Because clinical trials are conducted under widely varying conditions, adverse reaction rates observed in the clinical trials of a drug cannot be directly compared to rates in the clinical trials of another drug and may not reflect the rates observed in practice.

The safety of PYLERA plus omeprazole (OBMT) to eradicate Helicobacter pylori was assessed in an open-label, randomized, active-controlled clinical trial conducted in North America. The duration of treatment was 10 days with 147 patients exposed to PYLERA plus omeprazole (OBMT) and 152 exposed to control, consisting of omeprazole, amoxicillin, and clarithromycin (OAC). The age of the population in the study ranged from 18 to 75 years, with 59% male patients and 59% Caucasian patients.

Adverse drug reactions were reported in 58% of patients in the OBMT group and 59% of patients in the OAC group. There were no adverse reactions leading to discontinuation of the study during the clinical trial.

Adverse reactions with an incidence of ≥ 5% in OBMT group include abnormal feces, diarrhea, nausea, and headache. Adverse drug reactions with an incidence of ≥ 5% in OAC group include diarrhea, dysgeusia, dyspepsia, nausea and headache.

Table 2 lists adverse reactions with an incidence of ≥ 1%, in either groups (OBMT vs OAC) and in order of decreasing incidence for the OBMT group.

Table 2: Adverse reactions with an incidence of ≥ 1% from North American trial, [n (%)]
Preferred Term | OBMT [OBMT = Omeprazole + PYLERA] (n = 147) | OAC [OAC = Omeprazole + Amoxicillin + Clarithromycin;] (n = 152)
Gastrointestinal disorders
Abnormal feces [Dark stools [See Warnings and Precautions (5.7)].] | 23 (15.6%) | 7 (4.6%)
Nausea | 12 (8.2%) | 14 (9.2%)
Diarrhea | 10 (6.8%) | 20 (13.2%)
Abdominal Pain | 7 (4.8%) | 2 (1.3%)
Dyspepsia | 4 (2.7%) | 10 (6.6%)
Constipation | 2 (1.4%) | 5 (3.3%)
Dry Mouth | 2 (1.4%) | 1 (0.7%)
Flatulence | 0 | 4 (2.6%)
Glossitis | 0 | 2 (1.3%)
General disorders and administration site conditions
Asthenia | 5 (3.4%) | 2 (1.3%)
Infections and infestations
Vaginal infection | 4 (2.7%) | 3 (2.0%)
Nervous system disorders
Headache | 8 (5.4%) | 8 (5.3%)
Dysgeusia | 6 (4.1%) | 18 (11.8%)
Dizziness | 4 (2.7%) | 4 (2.6%)
Investigations
Laboratory test abnormal | 3 (2.0%) | 4 (2.6%)
Alanine aminotransferase increased | 2 (1.4%) | 0
Aspartate aminotransferase increased | 2 (1.4%) | 0
Renal and urinary disorders
Urine abnormality | 2 (1.4%) | 0
Skin and subcutaneous tissue disorders
Rash Maculo-Papular | 2 (1.4%) | 0
Rash | 1 (0.7%) | 3 (2.0%)
Pruritus | 0 | 4 (2.6%)

Adverse reactions with an incidence of <1% for OBMT group are: back pain, vomiting, tongue darkening [See Warnings and Precautions (5.7)]., anxiety, gastritis, gastroenteritis, myalgia, chest pain, increased appetite, blood creatine phosphokinase increased, malaise, somnolence, tachycardia, duodenal ulcer, visual disturbance, weight increased.

6.2 Postmarketing Experience

Additionally, the following adverse reactions, presented by system organ class in alphabetical order, have been identified during post approval use of PYLERA. Because these reactions are reported voluntarily from a population of uncertain size, it is not always possible to reliably estimate their frequency or establish a causal relationship to drug exposure.

- Gastrointestinal disorders: abdominal distention, eructation, flatulence
- General disorders and administration site conditions: chest discomfort, fatigue.
- Infections and infestations: candidiasis.

6.3 Other Important Adverse Reactions from Labeling for the Individual Components of PYLERA

Metronidazole

Blood and Lymphatic system disorders: reversible neutropenia, (leucopenia) in cases of prolonged treatment; rarely reversible thrombocytopenia however no persistent haematological abnormalities attributable to metronidazole have been observed [See Warnings and Precautions (5.4)].

Cardiac disorders: Flattening of the T-wave may be seen in electrocardiographic tracings.

Gastrointestinal disorders: Furry tongue, glositis, stomatitis; these may be associated with a sudden overgrowth of candida which may occur during therapy[See Warnings and Precautions (5.1)].

Immune system disorders: Urticaria, erythematous rash, Stevens - Johnson syndrome, toxic epidermal necrolysis, flushing, nasal congestion, and fever [See Contraindications (4.5)].

Metabolism and nutrition disorders: Cases of pancreatitis have been reported, which abated on withdrawal of the drug, have been reported.

Nervous system disorders: The most serious adverse reactions reported in patients treated with metronidazole have been convulsive seizures, encephalopathy, aseptic meningitis, optic and peripheral neuropathy, the latter characterized mainly by numbness or paresthesia of an extremity. In addition, patients have reported syncope, vertigo, incoordination, ataxia, confusion, dysarthria, irritability, depression, weakness and insomnia [See Warnings and Precautions (5.4)].

Tetracycline Hydrochloride

Blood and lymphatic system disorders: Hemolytic anemia, thrombocytopenia, thrombocytopenic purpura, neutropenia, and eosinophilia.

Gastrointestinal disorders: Rare instances of esophagitis and esophageal ulceration have been reported in patients taking the tetracycline-class antibiotics in capsule and tablet form. Most of the patients who experienced esophageal irritation took the medication immediately before going to bed. Permanent discoloration of teeth may be caused when tetracycline is used during tooth development. Enamel hypoplasia has also been reported [See Warnings and Precautions (5.1)].

Nervous system disorders: Pseudotumor cerebri (benign intracranial hypertension) in adults and bulging fontanels in infants. Tinnitus and myasthenic syndrome have been reported rarely.

Renal and urinary disorders: Rise in BUN has been reported and is possibly dose related [See Contraindications (4.4)].

Skin and subcutaneous tissue disorders: Exfoliative dermatitis and photosensitivity have been rarely reported [See Warnings and Precautions (5.5)].

7 DRUG INTERACTIONS

7.1 Methoxyflurane

Do not administer methoxyflurane to patients taking PYLERA. The concurrent use of tetracycline hydrochloride, a component of PYLERA, with methoxyflurane has been reported to result in fatal renal toxicity [See Contraindications (4.1)].

7.2 Disulfiram

Psychotic reactions have been reported in alcoholic patients who are using metronidazole, a component of PYLERA and disulfiram concurrently. PYLERA should not be given to patients who have taken disulfiram within the last 2 weeks [See Contraindications (4.2)].

7.3 Alcohol

Consumption of alcoholic beverages or administration of other products containing propylene glycol during treatment with PYLERA and for at least 3 days afterwards may cause a disulfiram-like reaction (abdominal cramps, nausea, vomiting, headaches, and flushing) due to the interaction between alcohol or propylene glycol and metronidazole, a component of PYLERA. Discontinue alcoholic beverage or other products containing propylene glycol during and for at least 3 days after therapy with PYLERA [See Contraindications (4.3)].

7.4 Oral Contraceptives

Concurrent use of PYLERA with oral contraceptive may make oral contraceptives less effective due to an interaction with the tetracycline component of PYLERA. Breakthrough bleeding has been reported. Women of child-bearing potential should use a different or additional form of contraception while taking PYLERA.

7.5 Anticoagulants

PYLERA may alter the anticoagulant effects of warfarin and other oral coumarin anticoagulants. Metronidazole has been reported to potentiate the anticoagulant effect of warfarin, and other oral coumarin anticoagulants, resulting in a prolongation of prothrombin time. Tetracycline has been shown to depress plasma prothrombin activity. Prothrombin time, International Normalized Ratio (INR), or other suitable anticoagulation tests should be closely monitored if PYLERA is administered concomitantly with warfarin. Patients should also be monitored for evidence of bleeding.

7.6 Lithium

In patients stabilized on relatively high doses of lithium, short-term use of PYLERA may cause elevation of serum lithium concentrations and signs of lithium toxicity due to the interaction between metronidazole and lithium. Serum lithium and serum creatinine concentrations should be monitored several days after beginning treatment with PYLERA to detect any increase that may precede clinical symptoms of lithium toxicity.

7.7 Antacids, Multivitamins, or Dairy Products

The absorption of PYLERA may be reduced if administered with antacids containing aluminium, calcium, or magnesium; preparations containing iron, zinc, or sodium bicarbonate; or milk or dairy products due to the interaction between these products and tetracycline. These products should not be consumed concomitantly with PYLERA. However, the clinical significance of reduced tetracycline systemic exposure is unknown as the relative contribution of systemic versus local antimicrobial activity against Helicobacter pylori has not been established.

7.8 Penicillin

Bacteriostatic drugs, such as the tetracycline class of antibiotics, may interfere with the bactericidal action of penicillin; therefore, penicillin should not be used concomitantly with PYLERA.

7.9 Inhibitors of CYP450 liver enzymes

The simultaneous administration of PYLERA and drugs that inhibit microsomal liver enzymes, such as cimetidine, may result in a prolonged half-life and decreased plasma clearance of metronidazole.

7.10 Inducers of CYP450 liver enzymes

The simultaneous administration of PYLERA and drugs that induce microsomal liver enzymes, such as phenytoin or phenobarbital, may accelerate the elimination of metronidazole, resulting in reduced plasma concentrations of metronidazole. Impaired clearance of phenytoin has also been reported in this situation. Monitor phenytoin concentrations during treatment with PYLERA.

8 USE IN SPECIFIC POPULATIONS

8.1 Pregnancy

Pregnancy Category D [See Warnings and Precautions (5.1)]

PYLERA contains bismuth subcitrate potassium, metronidazole, and tetracycline hydrochloride. There are no adequate and well-controlled studies of Pylera in pregnant women. However, tetracycline can cause fetal harm when administered to a pregnant woman. The use of tetracycline during the second and third trimester pregnancy can cause permanent discoloration of the teeth (yellow-gray brown) and possibly inhibit bone development. Administration of oral tetracycline to pregnant animals at various doses resulted in yellow fluorescence in teeth and bones. If PYLERA is used during pregnancy, or if the patient becomes pregnant while taking PYLERA, the patient should be apprised of the potential hazard to the fetus.

The available human and animal data are summarized below for each of PYLERA's active ingredients:

Tetracycline

Published case reports have described the yellowing of bones and teeth in human infants exposed to tetracycline during the second and third trimester of pregnancy. The yellowing is caused by the direct deposition of tetracycline during the mineralization process. The discoloration is more common during long-term use of the drug but has also been observed following repeated short-term courses. All tetracyclines form a stable calcium complex in any bone forming tissue. A decrease in fibula growth rate was observed in premature infants given oral tetracycline in doses of 25 mg/kg every six hours. The effect resolved when the drug was discontinuted. One long-term follow-up study in children exposed to tetracycline in-utero showed no adverse effects on bone growth and development.

Tetracycline administered during pregnancy at high doses (> 2 g IV) was associated with rare but serious cases of maternal hepatotoxicity. This syndrome may result in stillborn or premature birth due to maternal pathology [See Warnings and Precautions (5.2)]

Results of animal studies indicate that tetracycline crosses the placenta, is found in fetal tissues, and can have toxic effects on the developing fetus (often related to reversible retardation of skeletal development). Evidence of embryotoxicity has also been noted in animals treated early in pregnancy. Multiple studies of limited design were conducted with pregnant and lactating female rats that resulted in fetuses and neonates with yellow discoloration of bones and teeth.

Metronidazole

There are published data from case-control studies, cohort studies, and 2 meta-analyses that include more than 5000 pregnant women who used metronidazole during pregnancy. Many studies included first trimester exposures. One study showed an increased risk of cleft lip, with or without cleft palate, in infants exposed to metronidazole in-utero; however, these findings were not confirmed. In additon, more than ten randomized, placebo-controlled clinical trials enrolled more than 5000 pregnant women to assess the use of antibiotic treatment (including metronidazole) for bacterial vaginosis on the incidence of preterm delivery. Most studies did not show an increased risk for congenital anomalies or other adverse fetal outcomes following metronidazole exposure during pregnancy. These studies conducted to assess the risk of infant cancer following metronidazole exposure during pregnancy did not show an increased risk; however, the ability of these studies to detect such a signal was limited.

Metronidazole crosses the placental barrier and its effects on the human fetal organogenesis are not known. No fetotoxicity was observed when metronidazole was administered orally to pregnant mice at 10 mg/kg/day, approximately 5 percent of the indicated human dose (1500 mg/day) based on body surface area; however in a single small study where the drug was administered intraperitoneally, some intrauterine deaths were observed. The relationship of these findings to the drug is unknown.

Bismuth subcitrate potassium

Animal reproductive studies have not been conducted with bismuth subcitrate potassium. It is also not known whether bismuth subcitrate potassium can cause fetal harm when administered to a pregnant women or can affect reproduction capacity.

8.3 Nursing Mothers

PYLERA contains bismuth subcitrate potassium, metronidazole, and tetracycline hydrochloride. Metronidazole is present in human milk at concentrations similar to maternal serum levels, and infant serum levels can be close to or comparable to infant therapeutic levels. Because of the potential for tumorigenicity shown for metronidazole in animal studies, a decision should be made whether to discontinue nursing or to discontinue metronidazole, taking into account the importance of the therapy to the mother. Alternatively, a nursing mother may choose to pump and discard human milk for the duration of PYLERA therapy, and for 24 hours after therapy ends and feed her infant stored human milk or formula.

Tetracycline is present in human milk at concentrations similar to maternal serum levels; however, it binds with calcium in human milk. Data indicate that oral absorption of tetracycline in infants is low due to the calcium binding in human milk. It is not known whether bismuth subcitrate potassium is excreted in human milk.

8.4 Pediatric Use

Safety and effectiveness of PYLERA in pediatric patients infected with Helicobacter pylori have not been established.

Tetracycline use in children may cause permanent discoloration of the teeth. Enamel hypoplasia has also been reported. PYLERA should not be used in children up to 8 years of age [See Warnings and Precautions (5.3)].

8.5 Geriatric Use

Of the 324 patients who received PYLERA in clinical studies, 40 were ≥ 65 years old. Clinical studies of PYLERA did not include sufficient numbers of patients aged 65 and over to determine whether they respond differently than younger patients. Other reported clinical experience has not identified differences in responses between the elderly and younger patients. In general, elderly patients may have a greater frequency of decreased hepatic, renal, or cardiac function, and concomitant diseases or other drug therapies. Bismuth subcitrate potassium, a component of PYLERA, is known to be substantially excreted by the kidney, and the risk of adverse reactions may be greater in patients with impaired renal function. Because elderly patients are more likely to have decreased renal function, additional monitoring may be required [See Contraindications (4.4)].

8.6 Renal Impairment

The antianabolic action of the tetracyclines may cause an increase in blood urea nitrogen (BUN). While this is not a problem in those with normal renal function, in patients with severe renal impairment, higher serum concentrations of tetracycline may lead to azotemia, hyperphosphatemia, and acidosis [See Contraindications (4.4)]

8.7 Hepatic Impairment

Patients with severe hepatic disease metabolize metronidazole slowly, with resultant accumulation of metronidazole and its metabolites in plasma. Use PYLERA with caution in patients with hepatic impairment.

10 OVERDOSAGE

In case of an overdose, patients should contact a physician, poison control center, or emergency room. There is neither a pharmacological basis nor data suggesting an increased toxicity of the combination compared to individual components.

11 DESCRIPTION

PYLERA capsules are a combination antimicrobial product containing bismuth subcitrate potassium, metronidazole, and tetracycline hydrochloride for oral administration. Each size 0 elongated capsule contains:

- bismuth subcitrate potassium, 140 mg
- metronidazole, 125 mg
- smaller capsule (size 3) containing tetracycline hydrochloride, 125 mg

Tetracycline hydrochloride is encapsulated within a smaller capsule to create a barrier to avoid contact with bismuth subcitrate potassium.

Each PYLERA capsule contains the following inactive ingredients: Magnesium Stearate NF, Lactose Monohydrate NF, Talc USP, Gelatin USP, and Titanium Dioxide NF. Printed in red ink.

Bismuth subcitrate potassium is a white or almost white powder. It is a soluble, complex bismuth salt of citric acid. The schematized empirical molecular formula of bismuth subcitrate potassium is Bi (Citrate)2K5●3 H2O. The equivalent theoretical molecular formula is BiC12H14K5O17. The molecular mass of the theoretical molecular formula of a single unit of bismuth subcitrate potassium is 834.71.

Metronidazole is a white to pale yellow crystalline powder. Metronidazole is 2-methyl-5-nitroimidazole-1-ethanol, with a molecular formula of C6H9N3O3 and the following structural formula:

Molecular weight: 171.2

Tetracycline hydrochloride is a yellow, odorless, crystalline powder. Tetracycline hydrochloride is stable in air, but exposure to strong sunlight causes it to darken. Tetracycline hydrochloride is (4S,4aS,5aS,6S,12aS)-4-(dimethylamino)-1,4,4a,5,5a,6,11,12a-octahydro-3,6,10,12,12a-penta-hydroxy-6-methyl-1,11-dioxo-2-naphthacenecarboxamide hydrochloride, with a molecular formula of C22H24N2O8●HCl and the following structural formula:

Molecular weight: 480.90

12 CLINICAL PHARMACOLOGY

12.1 Mechanism of Action

PYLERA, a combination of bismuth subcitrate potassium, metronidazole and tetracycline hydrochloride is an antibacterial agent [See Clinical Pharmacology (12.4)].

12.3 Pharmacokinetics

The pharmacokinetics of the individual components of PYLERA, bismuth subcitrate potassium, metronidzole, tetracycline hydrochloride, are summarized below. In addition, two studies on PYLERA were conducted to determine the effect of co-administration on the pharmacokinetics of the components.

Bismuth Subcitrate Potassium (Bismuth)

Absorption and Distribution

Orally absorbed bismuth is distributed throughout the entire body. Bismuth is highly bound to plasma proteins (>90%).

Metabolism and Excretion

The elimination half-life of bismuth is approximately 5 days in both blood and urine. Elimination of bismuth is primarily through urinary and biliary routes. The rate of renal elimination appears to reach steady state 2 weeks after treatment discontinuation with similar rates of elimination at 6 weeks after discontinuation. The average urinary elimination of bismuth is 2.6% per day in the first two weeks after discontinuation (urine drug concentrations 24 to 250 mcg/mL) suggesting tissue accumulation and slow elimination.

Metronidazole

Absorption and Distribution

Following oral administration, metronidazole is well absorbed, with peak plasma concentrations occurring between 1 and 2 hours after administration. Plasma concentrations of metronidazole are proportional to the administered dose, with oral administration of 500 mg producing a peak plasma concentration of 12 mcg/mL.

Metronidazole appears in the plasma mainly as unchanged compound with lesser quantities of the 2-hydroxymethyl metabolite also present. Less than 20% of the circulating metronidazole is bound to plasma proteins. Metronidazole also appears in cerebrospinal fluid, saliva, and breast milk in concentration similar to those found in plasma.

Metabolism and Excretion

The average elimination half-life of metronidazole in normal volunteers is 8 hours. The major route of elimination of metronidazole and its metabolites is via the urine (60% to 80% of the dose), with fecal excretion accounting for 6% to 15% of the dose. The metabolites that appear in the urine result primarily from side-chain oxidation [1-(β-hydroxyethyl) 2-hydroxymethyl-5-nitroimidazole and 2-methyl-5-nitroimidazole-1-yl-acetic acid] and glucuronide conjugation, with unchanged metronidazole accounting for approximately 20% of the total. Renal clearance of metronidazole is approximately 10 mL/min/1.73m^2.

Decreased renal function does not alter the single dose pharmacokinetics of metronidazole. In patients with decreased liver function, plasma clearance of metronidazole is decreased.

Tetracycline Hydrochloride

Absorption, Distribution, Metabolism and Excretion

Tetracycline hydrochloride is absorbed (60%-90%) in the stomach and upper small intestine. The presence of food, milk or cations may significantly decrease the extent of absorption. In the plasma, tetracycline is bound to plasma proteins in varying degrees. It is concentrated by the liver in the bile and excreted in the urine and feces at high concentrations in biologically active form.

Tetracycline hydrochloride is distributed into most body tissues and fluids. It is distributed into the bile and undergoes varying degrees of enterohepatic recirculation. Tetracycline hydrochloride tends to localize in tumors, necrotic or ischemic tissue, liver and spleen and form tetracycline-calcium orthophosphate complexes at sites of new bone formation or tooth development. Tetracycline readily crosses the placenta and is excreted in high amounts in breast milk.

PYLERA Capsules

A comparative bioavailability study of metronidazole (375 mg), tetracycline hydrochloride (375 mg) and bismuth subcitrate potassium (420 mg, equivalent to 120 mg Bi2O3) administered as PYLERA or as 3 separate capsule formulations administered simultaneously was conducted in healthy male volunteers. The pharmacokinetic parameters for the individual drugs, when administered as separate capsule formulations or as PYLERA, are similar as shown in Table 3.

Table 3: Mean (%CV) Pharmacokinetic Parameters for Metronidazole, Tetracycline hydrochloride, and Bismuth Subcitrate Potassium in Healthy Volunteers (N=18)
 |  | Cmax (ng/mL) (%C.V. [C.V. – Coefficient Variation]) | AUCT (ng · h/mL) (%C.V.) | AUC∞ (ng · h/mL) (%C.V.)
Metronidazole | Metronidazole Capsule | 9044 (20) | 80289 (15) | 81849 (16)
 | PYLERA [PYLERA given as a single dose of 3 capsules] | 8666.3 (22) | 83018 (17) | 84413 (17)
Tetracycline | Tetracycline Capsules | 748.0 (40) | 9544 (55) | 9864 (53)
 | PYLERA | 774 (47) | 9674 (50) | 9987 (49)
Bismuth | Bismuth Capsule | 22 (123) | 47 (129) | 65.4 (113)
 | PYLERA | 17 (202) | 43 (191) | 57 (178)

Effect of Bismuth on the Bioavailability of Tetracycline Hydrochloride

There is an anticipated reduction in tetracycline hydrochloride systemic absorption due to an interaction with bismuth. The effect of a reduced tetracycline hydrochloride systemic exposure, due to an interaction with bismuth, on the clinical efficacy of PYLERA is not thought to be clinically meaningful as the contribution of systemic, as compared to local, antimicrobial activity against Helicobacter pylori has not been established.

Effect of Food on the Bioavailability of PYLERA

The pharmacokinetic parameters for metronidazole, tetracycline hydrochloride and bismuth were also determined when PYLERA was administered under fasting and fed conditions, as shown in Table 4. Food reduced the systemic absorption of all three PYLERA components, with AUC values for metronidazole, tetracycline hydrochloride and bismuth being reduced by 6%, 34% and 60%, respectively. Reduction in the absorption of all three PYLERA components in the presence of food is not considered to be clinically significant. PYLERA should be given after meals and at bedtime, in combination with omeprazole twice a day.

Table 4: Mean PYLERA Pharmacokinetic Parameters in Fasted and Fed States (N=18) [PYLERA given as a single dose of 3 capsules]
 | FED |  |  | FASTED
 | metronidazole | tetracycline | bismuth | metronidazole | tetracycline | bismuth
Cmax (ng/mL) (%C.V.) | 6835.0 (13) | 515.8 (36) | 1.7 (61) | 8666.3 (22) | 773.8 (47) | 16.7 (202)
Tmax (hours) [Tmax is expressed as median (range)] (range) | 3.0 (1.3 – 4.0) | 4.0 (2.5 – 5.0) | 3.5 (0.8 – 6.0) | 0.75 (0.5 - 3.5) | 3.3 (1.3 – 5.0) | 0.6 (0.5 – 1.7)
AUC∞(ng · h/mL) (%C.V.) | 79225.6 (18) | 5840.1 (312) | 18.4 (116) | 84413.6 (17) | 9986.7 (49) | 56.5 (178)

Effect of Omeprazole on the Bioavailability of Bismuth

The effect of omeprazole on bismuth absorption was assessed in 34 healthy volunteers given PYLERA (four times daily) with or without omeprazole (20 mg twice daily) for 6 days. In the presence of omeprazole, the extent of absorption of bismuth from PYLERA was significantly increased, compared to when no omeprazole was given (Table 5). Concentration-dependent neurotoxicity is associated with long-term use of bismuth and not likely to occur with short-term administration or at steady state concentrations below 50 ng/mL. One subject transiently achieved a maximum bismuth concentration (Cmax) higher than 50 ng/mL (73 ng/mL) following multiple dosing of PYLERA with omeprazole. The patient did not exhibit symptoms of neurotoxicity during the study. There is no clinical evidence to suggest that short-term exposure to bismuth Cmax concentrations above 50 ng/mL is associated with neurotoxicity.

Table 5: Mean Bismuth Pharmacokinetic Parameters following PYLERA Administration [PYLERA given as 3 capsules four times daily for 6 days with or without 20 mg omeprazole twice daily] With and Without Omeprazole (N=34)
Parameter | Without omeprazole |  | With omeprazole
Parameter | Mean | %C.V. [C.V. – Coefficient Variation] | Mean | %C.V.
Cmax(ng/mL) | 8.1 | 84 | 25.5 | 69
AUCT(ng · h/mL) | 48.5 | 28 | 140.9 | 42

12.4 Microbiology

Mechanism of Action

PYLERA, a combination of bismuth subcitrate potassium, metronidazole and tetracycline hydrochloride has antibacterial activity. Metronidazole is metabolized through reductive pathways into reactive intermediates that have cytotoxic action. Tetracycline hydrochloride interacts with the 30S subunit of the bacterial ribosome and inhibits protein synthesis. The antibacterial action of bismuth salts is not well understood.

Activity in vitro and in vivo

PYLERA plus omeprazole therapy has been shown to be active against most strains of Helicobacter pylori both in vitro and in clinical infections. [See Clinical Studies (14)].

Susceptibility Test Methods

Dilution techniques:

Susceptibility testing of Helicobacter pylori isolates was performed for metronidazole using agar dilution methodology according to CLSI^1 guidelines [See References (15)], and minimum inhibitory concentrations (MICs) were determined.

Susceptibility testing of Helicobacter pylori for metronidazole has not been standardized. No interpretive criteria have been established for testing metronidazole against H. pylori.

The clinical significance of metronidazole MIC values against H. pylori is unknown. In the North American study, pre-treatment metronidazole MIC values showed no correlation with clinical outcome in patients treated with PYLERA and omeprazole therapy.

13 NONCLINICAL TOXICOLOGY

13.1 Carcinogenesis, Mutagenesis, Impairment of Fertility

No long-term studies have been performed to evaluate the effect of PYLERA on carcinogenesis, mutagenesis, or impairment of fertility.

Bismuth Subcitrate Potassium

No carcinogenicity or reproductive toxicity studies have been conducted with bismuth subcitrate potassium. Bismuth subsalicylate did not show mutagenic potential in the NTP Salmonella plate assay.

Metronidazole

Metronidazole has shown evidence of carcinogenic activity in a number of studies involving chronic, oral administration in mice and rats. Prominent among the effects in the mouse was an increased incidence of pulmonary tumorigenesis. This has been observed in all six reported studies in that species, including one study in which the animals were dosed on an intermittent schedule (administration during every fourth week only). At the highest dose levels, (approximately 500 mg/kg/day, which is approximately 1.6 times the indicated human dose for a 60 kg adult based on body surface area), there was a statistically significant increase in the incidence of malignant liver tumors in male mice. Also, the published results of one of the mouse studies indicate an increase in the incidence of malignant lymphomas as well as pulmonary neoplasms associated with lifetime feeding of the drug. All these effects are statistically significant. Long-term, oral-dosing studies in the rat showed statistically significant increases in the incidence of various neoplasms, particularly in mammary and hepatic tumors, among female rats administered metronidazole over those noted in the concurrent female control groups. Two lifetime tumorigenicity studies in hamsters have been performed and reported to be negative. Although metronidazole has shown mutagenic activity in a number of in vitro assay systems, studies in mammals (in vivo) have failed to demonstrate a potential for genetic damage.

Fertility studies have been conducted with male rates and mice with divergent results. Metronidazole, at doses up to 400 mg/kg/day (approximately 3 times the indicated human dose based on mg/m^2) for 28 days, failed to produce any adverse effects on fertility and testicular function in male rats. In another study where rats were treated with up to 400 mg/kg/day for 8 weeks, there was severe degeneration of the seminiferous epithelium in the testes which was associated with a marked decrease in testicular spermatid counts and epididymal sperm counts and a marked decrease in fecundity. These effects were partially reversible.

Fertility studies were performed in male mice at doses up to six times the maximum human dose based upon mg/m^2 and have revealed no evidence of impaired fertility. Another fertility study was performed in male mice at oral doses of 500 mg/kg/day (approximately 2 times the indicated human dose based on mg/m^2 for 14 days. Metronidazole significantly decreased testes and epididymides weight, decreased sperm viability, and increased the incidence of abnormal sperm. The viability of sperm was normal by 2 months after the start of the treatment.

Tetracycline hydrochloride

There has been no evidence of carcinogenicity for tetracycline hydrochloride in studies conducted with rats and mice. Some related antibiotics (oxytetracycline, minocycline) have shown evidence of oncogenic activity in rats.

There was evidence of mutagenicity by tetracycline hydrochloride in two in vitro mammalian cell assay systems (L51784y mouse lymphoma and Chinese hamster lung cells).

Tetracycline hydrochloride had no effect on fertility when administered in the diet to male and female rats at a daily intake of 25 times the human dose.

14 CLINICAL STUDIES

14.1 Eradication of Helicobacter pylori in Patients with Active Duodenal Ulcer or History of Duodenal Ulcer Disease

An open-label, parallel group, active-controlled, multicenter study in Helicobacter pylori positive patients with current duodenal ulcer or a history of duodenal ulcer disease was conducted in the United States and Canada (the North American Study).

Patients were randomized to one of the following 10-day treatment regimens:

- Three (3) PYLERA capsules four times daily, after meals and at bedtime plus 20 mg omeprazole twice a day after the morning and evening meals (OBMT).
- Clarithromycin 500 mg plus 1000 mg amoxicillin plus 20 mg omeprazole twice a day before the morning and evening meals (OAC).

H. pylori eradication rates, defined as two negative ^13C-urea breath tests performed at 4 and 8 weeks post-therapy are shown in Table 6 for OBMT and OAC. The eradication rates for both groups were found to be similar using either the Per Protocol (PP) or Modified Intent-to-Treat (MITT) populations.

Table 6: Helicobacter pylori Eradication at 8 Weeks after 10 Day Treatment Regimen Percent (%) of Patients Cured [95% Confidence Interval] (Number of Patients)
 | Treatment Group |  | Difference
 | OBMT [OBMT: Omeprazole + PYLERA (bismuth subcitrate potassium / metronidazole / tetracycline hydrochloride)] | OAC [OAC: Omeprazole + Amoxicillin + Clarithromycin] [Results for OAC treatment represent all isolates regardless of clarithromycin susceptibility. Eradication rates for clarithromycin susceptible organisms, as defined by an MIC ≤ 0.25 μg/mL, were 94.6% and 92.1% for the PP and MITT analysis, respectively. Eradication rates for clarithromycin non-susceptible organisms, as defined by an MIC ≥ 0.5 μg/mL, were 23.1% and 21.4% for the PP and MITT analysis, respectively.]
Per Protocol [Patients were included in the PP analysis if they had H. pylori infection documented at baseline, defined as a positive ^13C-UBT plus histology or culture, had at least one endoscopically verified duodenal ulcer ≥ 0.3 cm at baseline or had a documented history of duodenal ulcer disease, and were not protocol violators. Additionally, if patients dropped out of the study due to an adverse event related to the study drug, they were included in the evaluable analysis as failures of therapy.] | 92.5% [87.8, 97.2] (n=120) | 85.7% [76.9, 91.8] (n=126) | 6.8 [-0.9, 14.5]
Modified Intent-to-Treat [Patients were included in the MITT analysis if they had documented H. pylori infection at baseline as defined above, and had at least one documented duodenal ulcer at baseline or had a documented history of duodenal ulcer disease, and took at least one dose of study medication. All dropouts were included as failures of therapy.] | 87.7% [82.2, 93.2] (n=138) | 83.2% [77.0, 89.5] (n=137) | 4.5 [-3.9, 12.8]

15 REFERENCES

1. Clinical and Laboratory Standards Institute. Methods for Dilution Antimicrobial Susceptibility Tests for Bacteria that Grow Aerobically; Approved Standard - - Eight edition. Clinical and Laboratory standards Institute document M7-A8, Vol. 29, No. 2, CLSI, Wayne, PA, January 2009.

16 HOW SUPPLIED/STORAGE AND HANDLING

PYLERA is supplied as a white opaque capsule containing 140 mg bismuth subcitrate potassium, 125 mg metronidazole, and 125 mg tetracycline hydrochloride, with the Axcan Pharma logo printed on the body and “BMT” printed on the cap. PYLERA is supplied in:

Bottles of 120 | NDC 54868-6151-0

Storage

Store at controlled room temperature [68° to 77°F or 20° to 25°C]

Relabeling of "Additional Barcode" label by:

Physicians Total Care, Inc.

Tulsa, OK 74146

17 PATIENT COUNSELING INFORMATION

17.1 Pregnant Women

Advise pregnant women that PYLERA capsules can cause fetal harm due to the tetracycline it contains. Tetracycline use during the second and third trimesters of pregnancy can cause permanent discoloraton of the teeth (yellow-gray brown) and may inhibit bone development [See Warnings and Precautions (5.1)] and [See Use in Specific Populations (8.3)].

17.2 Human Milk Feeding

Advise women to avoid feeding their infants with their milk during PYLERA treatment. Women should either discontinue feeding or pump and discard their milk during treatment and for 24 hours after the last dose [See Use in Specific Populations (8.3)].

17.3 Hypersensitivity

Inform patients that PYLERA may cause allergic reactions and to discontinue PYLERA at the first sign of urticaria, erythematous rash, flushing, and fever or other symptoms of an allergic reaction [See Contraindications (4.4)].

17.4 Central Nervous System Effects

Inform patients of the risk of central and peripheral nervous system effects with PYLERA and to discontinue PYLERA and report immediately to their health-care provider if any neurologic symptoms occur [See Warnings and Precautions (5.4)].

17.5 Photosensitivity

Avoid exposure to sun or sun lamps while taking PYLERA [See Warnings and Precautions (5.6)].

17.6 Drug Interactions

Advise patients to report to their health-care provider the use of any other medications while taking PYLERA. The administration of any of the following drugs with PYLERA may result in clinically significant adverse reactions or insufficient drug efficacies [See Contraindications (4)] ;Drug Interactions (7)] :

- Methoxyflurane
- Disulfiram
- Alcoholic Beverages, or Products Containing Propylene Glycol
- Oral Contraceptives
- Anticoagulants
- Lithium
- Antacids, Multivitamins, or Dairy Products

17.7 Darkening of the Tongue and/or Stool

Inform patients that PYLERA may cause temporary and harmless darkening of the tongue and/or black stool generally reversible within several days after treatment is stopped. Stool darkening should not be confused with melena (blood in the stool) [See Warnings and Precautions (5.7)].

17.8 Dosing Information

Inform patients that each dose of PYLERA includes 3 capsules. Each dose of all 3 capsules should be taken 4 times a day, after meals and at bedtime for 10 days. One omeprazole 20 mg capsule should be taken twice a day with PYLERA after the morning and evening meal for 10 days.

Missed doses can be made up by continuing the normal dosing schedule until the medication is gone. They should not take double doses. If more than 4 doses are missed, contact their health-care provider [See Dosage and Administration (2)].

17.9 Administration with Fluids

Instruct patients to swallow the PYLERA capsules whole with a full glass of water (8 ounces). Ingestion of adequate amounts of fluid, particularly with the bedtime dose, is recommended to reduce the risk of esophageal irritation and ulceration by tetracycline hydrochloride [See Dosage and Administration (2)].

17.10 Antibacterial Resistance

Patients should be counseled that antibacterial drugs including PYLERA should only be used to treat bacterial infections. They do not treat viral infections (e.g., the common cold). When PYLERA is prescribed to treat a bacterial infection, patients should be told that although it is common to feel better early in the course of therapy, the medication should be taken exactly as directed. Skipping doses or not completing the full course of therapy may (1) decrease the effectiveness of the immediate treatment and (2) increase the likelihood that bacteria will develop resistance and will not be treatable by PYLERA or other antibacterial drugs in the future.

Principal Display Panel

Pylera